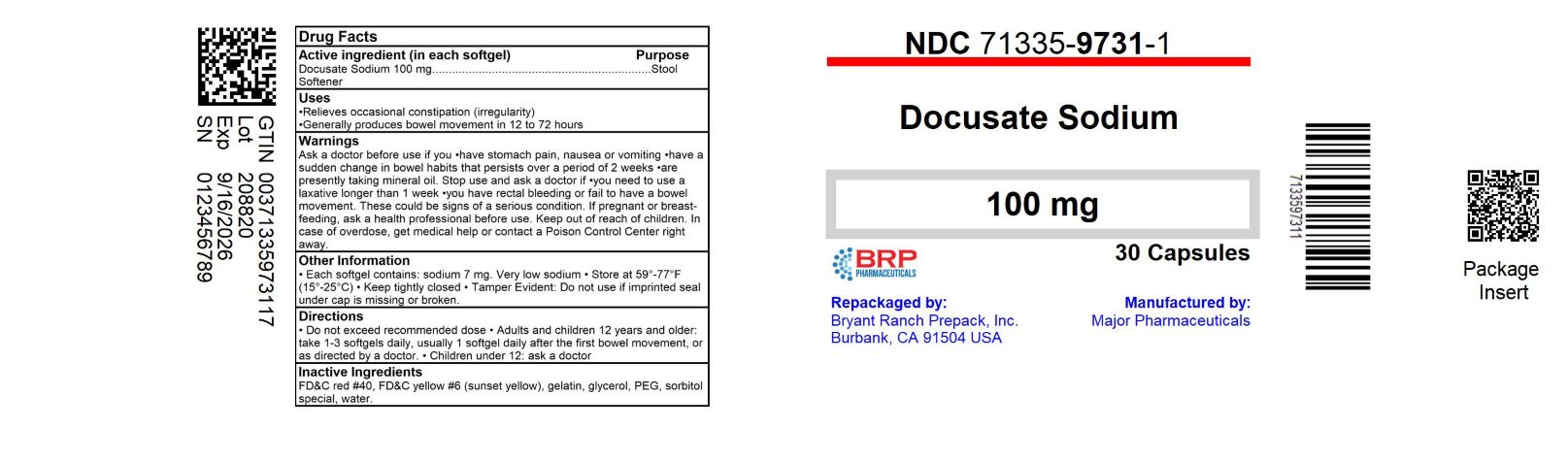 DRUG LABEL: Stool Softener Laxative
NDC: 71335-9731 | Form: CAPSULE, LIQUID FILLED
Manufacturer: Bryant Ranch Prepack
Category: otc | Type: HUMAN OTC DRUG LABEL
Date: 20240906

ACTIVE INGREDIENTS: DOCUSATE SODIUM 100 mg/1 1
INACTIVE INGREDIENTS: FD&C RED NO. 40; FD&C YELLOW NO. 6; GELATIN, UNSPECIFIED; POLYETHYLENE GLYCOL, UNSPECIFIED; PROPYLENE GLYCOL; WATER; SORBITOL; GLYCERIN; CITRIC ACID MONOHYDRATE; SORBITAN

DRUG FACTS

Active ingredient (in each softgel)

Docusate sodium 100 mg

Purpose

Stool softener laxative

Uses

- relieves occasional constipation (irregularity)
- generally produces bowel movement in 12 to 72 hours

Warnings

Do not use

if you are presently taking mineral oil, unless told to do so by a doctor.

Ask a doctor before use if you have

- stomach pain
- nausea
- vomiting
- noticed a sudden change in bowel habits that lasts over 2 weeks

Stop use and ask a doctor if

- you have rectal bleeding or fail to have a bowel movement after use of a laxative. These could be signs of a serious condition.
- you need to use a stool softener laxative for more than 1 week

If pregnant or breast-feeding,

ask a health care professional before use.

Keep out of reach of children.

In case of overdose, get medical help or contact a Poison Control Center (1-800-222-1222) right away.

Directions

- take only by mouth. Doses may be taken as a single daily dose or in divided doses.

adults and children 12 years and over | take 1-3 softgels daily
children 2 to under 12 years of age | take 1 softgel daily
children under 2 years | ask a doctor

Other information

- each softgel contains: sodium 7 mg
- store at 25ºC (77ºF); excursion permitted between 15-30ºC (59-86ºF)

Inactive ingredients

citric acid, FD&C red #40, FD&C yellow #6, gelatin, glycerin, polyethylene glycol, propylene glycol, purified water, sorbitol special, white edible ink

Questions or comments?

Call 1-877-753-3935 Monday-Friday 9AM-5PM EST

HOW SUPPLIED

Docusate Sodium 100 mg

- NDC: 71335-9731-1: 30 Capsules in a BOTTLE
- NDC: 71335-9731-2: 100 Capsules in a BOTTLE
- NDC: 71335-9731-3: 60 Capsules in a BOTTLE
- NDC: 71335-9731-4: 120 Capsules in a BOTTLE
- NDC: 71335-9731-5: 90 Capsules in a BOTTLE
- NDC: 71335-9731-6: 180 Capsules in a BOTTLE
- NDC: 71335-9731-7: 10 Capsules in a BOTTLE
- NDC: 71335-9731-8: 28 Capsules in a BOTTLE
- NDC: 71335-9731-9: 56 Capsules in a BOTTLE
- NDC: 71335-9731-0: 18 Capsules in a BOTTLE

Repackaged/Relabeled by:
Bryant Ranch Prepack, Inc.
Burbank, CA 91504

PACKAGE LABEL

Docusate Sodium 100 mg Capsules